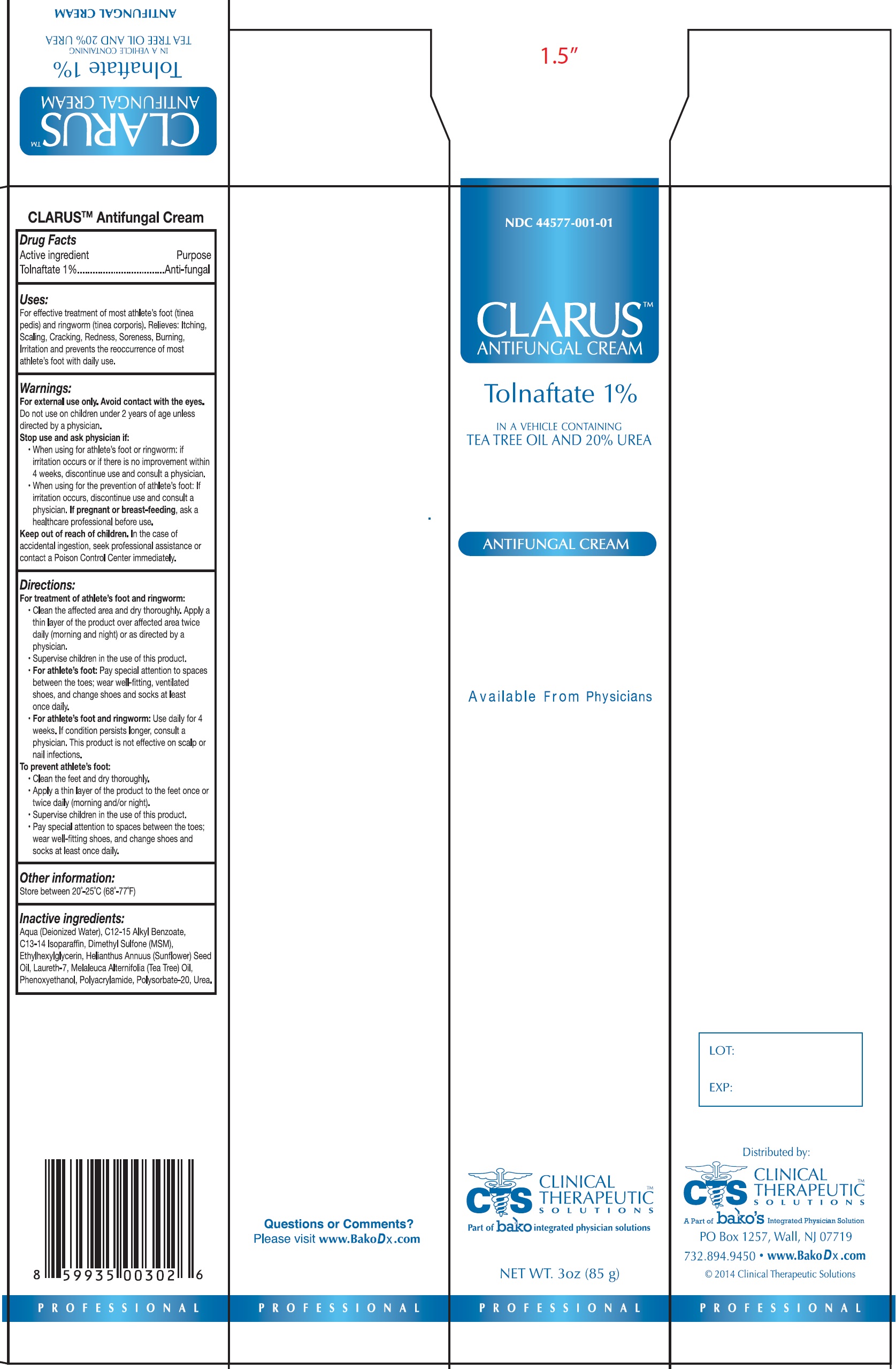 DRUG LABEL: CLARUS Antifungal
NDC: 44577-470 | Form: CREAM
Manufacturer: Clinical Therapeutic Solutions
Category: otc | Type: HUMAN OTC DRUG LABEL
Date: 20240228

ACTIVE INGREDIENTS: TOLNAFTATE 10 mg/1 g
INACTIVE INGREDIENTS: WATER; ALKYL (C12-15) BENZOATE; C13-14 ISOPARAFFIN; DIMETHYL SULFONE; ETHYLHEXYLGLYCERIN; SUNFLOWER OIL; LAURETH-7; TEA TREE OIL; PHENOXYETHANOL; POLYSORBATE 20; UREA

CLARUS Antifungal Cream

Active Ingredient

Tolnaftate 1 %

Purpose

Anti-fungal

Uses:

For effective treatment of most athlete's foot (tinea pedis) and ringworm (tinea corporis). Relieves: Itching, Scaling, Cracking, Redness, Soreness, Burning, Irritation and prevents the reoccurrence of most athlete's foot with daily use.

Warnings:

For external use only. Avoid contact with the eyes.

Do not use

on children under 2 years of age unless directed by a physician.

Stop use and ask physician if:

- When using for athlete's foot or ringworm: if irritation occurs or if there is no improvement within 4 weeks, discontinue use and consult a physician.
- When using for prevention of athlete's foot: If irritation occurs, discontinue use and consult a physician.

If pregnant or breast-feeding,

ask a healthcare professional before use.

Keep out of reach of children.

In the case of accidental ingestion, seek professional assistance or contact a Poison Control Center immediately.

Directions:

For treatment of athlete's foot and ringworm:

- Clean the affected area and dry thoroughly. Apply a thin layer of the product over affected area twice daily (morning and night) or as directed by a physician.
- Supervise children in the use of this product.
- For athlete's foot:Pay special attention to spaces between the toes; wear well-fitting, ventilated shoes, and change shoes and socks at least once daily.
- For athlete's foot and ringworm:Use daily for 4 weeks. If condition persists longer, consult a physician. This product is not effective on scalp or nail infections.
- To prevent athlete's foot:

- Clean the feet and dry thoroughly.
- Apply a thin layer of the product to the feet once or twice daily (morning and/or night).
- Supervise children in the use of this product.
- Pay special attention to spaces between the toes; wear well-fitting shoes, and change shoes and socks at least once daily.

Other information:

Store between 20º -25ºC (68º -77ºF)

Inactive ingredients:

Aqua (Deionized Water), C12-15 Alkyl Benzoate, C13-14 Isoparafin, Dimethyl Sulfone (MSM), Ethylhexylglycerin, Helianthus Annuus (Sunflower) Seed Oil, Laureth-7, Melaleuca Alternifolia (Tea Tree) Oil, Phenoxyethanol, Polyacrylamide, Polysorbate-20, Urea.